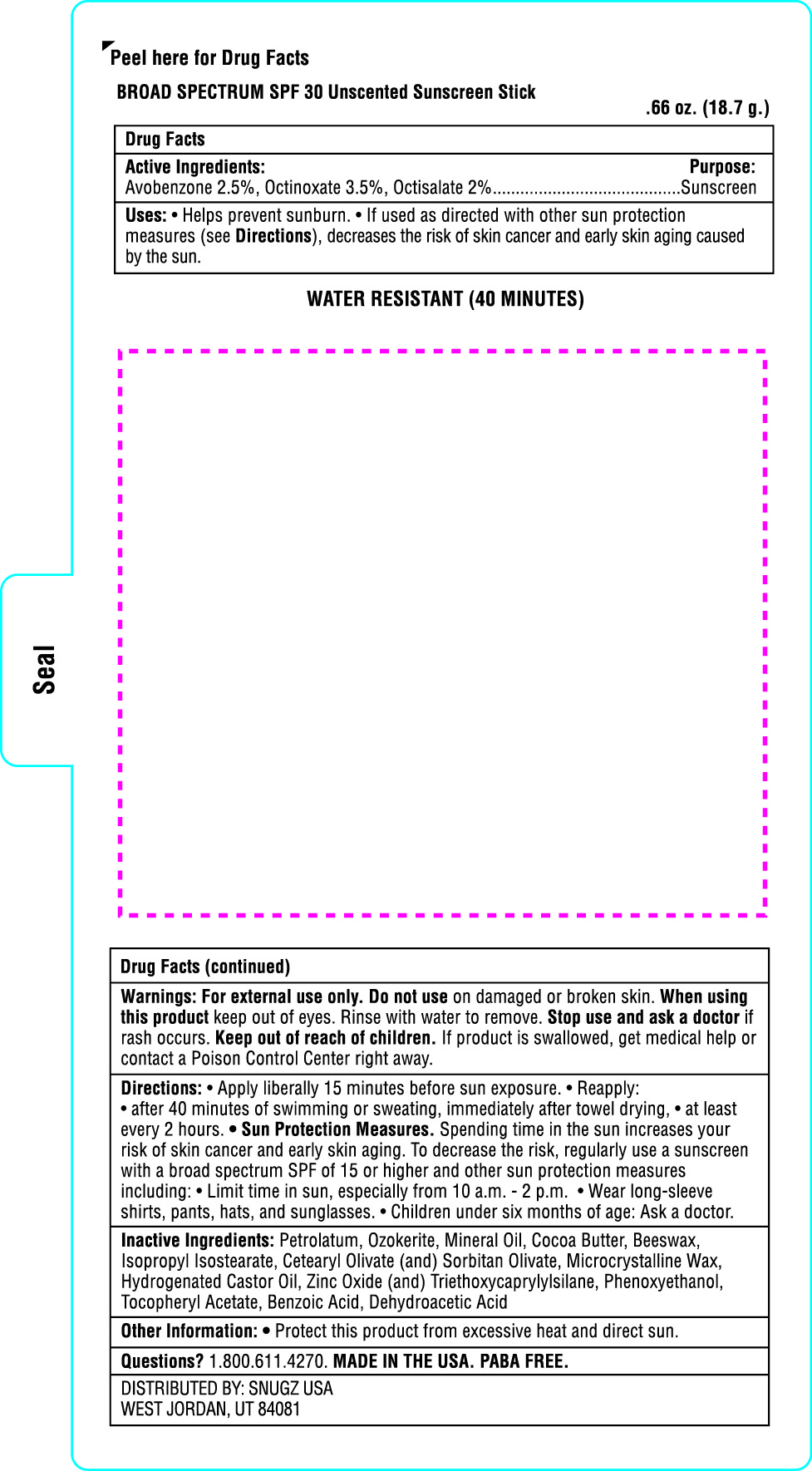 DRUG LABEL: SnugZ SPF 50 Sunscreen Stick
NDC: 76309-500 | Form: STICK
Manufacturer: SnugZ/USA, LLC
Category: otc | Type: HUMAN OTC DRUG LABEL
Date: 20191112

ACTIVE INGREDIENTS: OCTISALATE 0.561 g/18.7 g; ZINC OXIDE 0.187 g/18.7 g; OCTINOXATE 0.561 g/18.7 g
INACTIVE INGREDIENTS: PETROLATUM

ZSUN - SPF 50 Sunstick